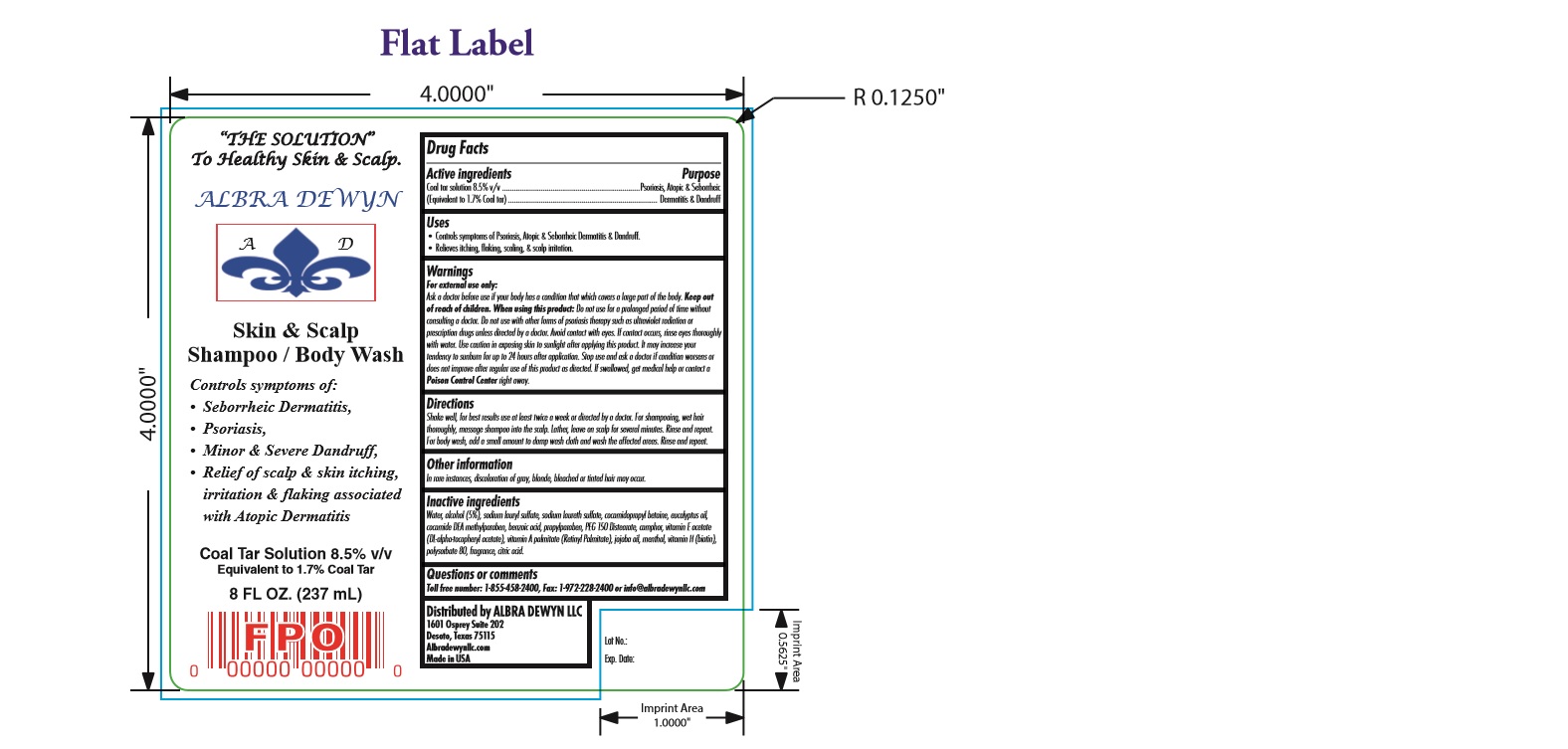 DRUG LABEL: Skin and scalp
NDC: 59151-645 | Form: SHAMPOO
Manufacturer: Albra Dewyn LLC
Category: otc | Type: HUMAN OTC DRUG LABEL
Date: 20160914

ACTIVE INGREDIENTS: COAL TAR 17 mg/1 mL
INACTIVE INGREDIENTS: EUCALYPTUS OIL; COCAMIDOPROPYL DIMETHYLAMINE PROPIONATE; PEG-150 DISTEARATE; CAMPHOR (NATURAL); JOJOBA OIL; BIOTIN; POLYSORBATE 80; WATER; ALCOHOL; SODIUM LAURYL SULFATE; SODIUM LAURETH SULFATE; COCAMIDOPROPYL BETAINE; METHYLPARABEN; BENZOIC ACID; PROPYLPARABEN; MENTHOL; CITRIC ACID MONOHYDRATE; .ALPHA.-TOCOPHEROL ACETATE, DL-; VITAMIN A PALMITATE

Skin & Scalp Shampoo / Body Wash

DRUG FACTS

Active ingredients Purpose
Coal tar solution 8.5% v/v .......................................................................Psoriasis, Atopic & Seborrheic
(Equivalent to 1.7% Coal tar)............................................................................. Dermatitis & Dandruff

USES

Controls symptoms of Psoriasis, Atopic & Seborrheic Dermatitis & Dandruff. • Relieves itching, flaking, scaling, & scalp irritation.

WARNINGS

For external use only: Ask a doctor before use if your body has a condition that which covers a large part of the body. Keep out of reach of children. When using this product: Do not use for a prolonged period of time without consulting a doctor. Do not use with other forms of psoriasis therapy such as ultraviolet radiation or prescription drugs unless directed by a doctor. Avoid contact with eyes. If contact occurs, rinse eyes thoroughly with water. Use caution in exposing skin to sunlight after applying this product. It may increase your tendency to sunburn for up to 24 hours after application. Stop use and ask a doctor if condition worsens or does not improve after regular use of this product as directed. If swallowed, get medical help or contact a Poison Control Center right away.

DIRECTIONS

Shake well, for best results use at least twice a week or directed by a doctor. For shampooing, wet hair thoroughly, massage shampoo into the scalp. Lather, leave on scalp for several minutes. Rinse and repeat. For body wash, add a small amount to damp wash cloth and wash the affected areas. Rinse and repeat

PURPOSE

Controls symptoms of: • Seborrheic Dermatitis, • Psoriasis, • Minor & Severe Dandruff, • Relief of scalp & skin itching, irritation & flaking associated with Atopic Dermatitis

OTHER INFORMATION

In rare instances, discoloration of gray, blonde, bleached or tinted hair may occur.

INactive

Inactive ingredients Water, alcohol (5%), sodium lauryl sulfate, sodium laureth sulfate, cocamidopropyl betaine, eucalyptus oil,
cocamide DEA methylparaben, benzoic acid, propylparaben, PEG 150 Distearate, camphor, vitamin E acetate (DL-alpha-tocopheryl acetate),
vitamin A palmitate (Retinyl Palmitate), jojoba oil, menthol, vitamin H (biotin), polysorbate 80, fragrance, citric acid.

Questions or comments Toll free number: 1-855-458-2400, Fax: 1-972-228-2400 or info@albradewynllc.com

INDICATIONS AND USAGE

Uses • Controls symptoms of Psoriasis, Atopic & Seborrheic Dermatitis & Dandruff. • Relieves itching, flaking, scaling, & scalp irritation.